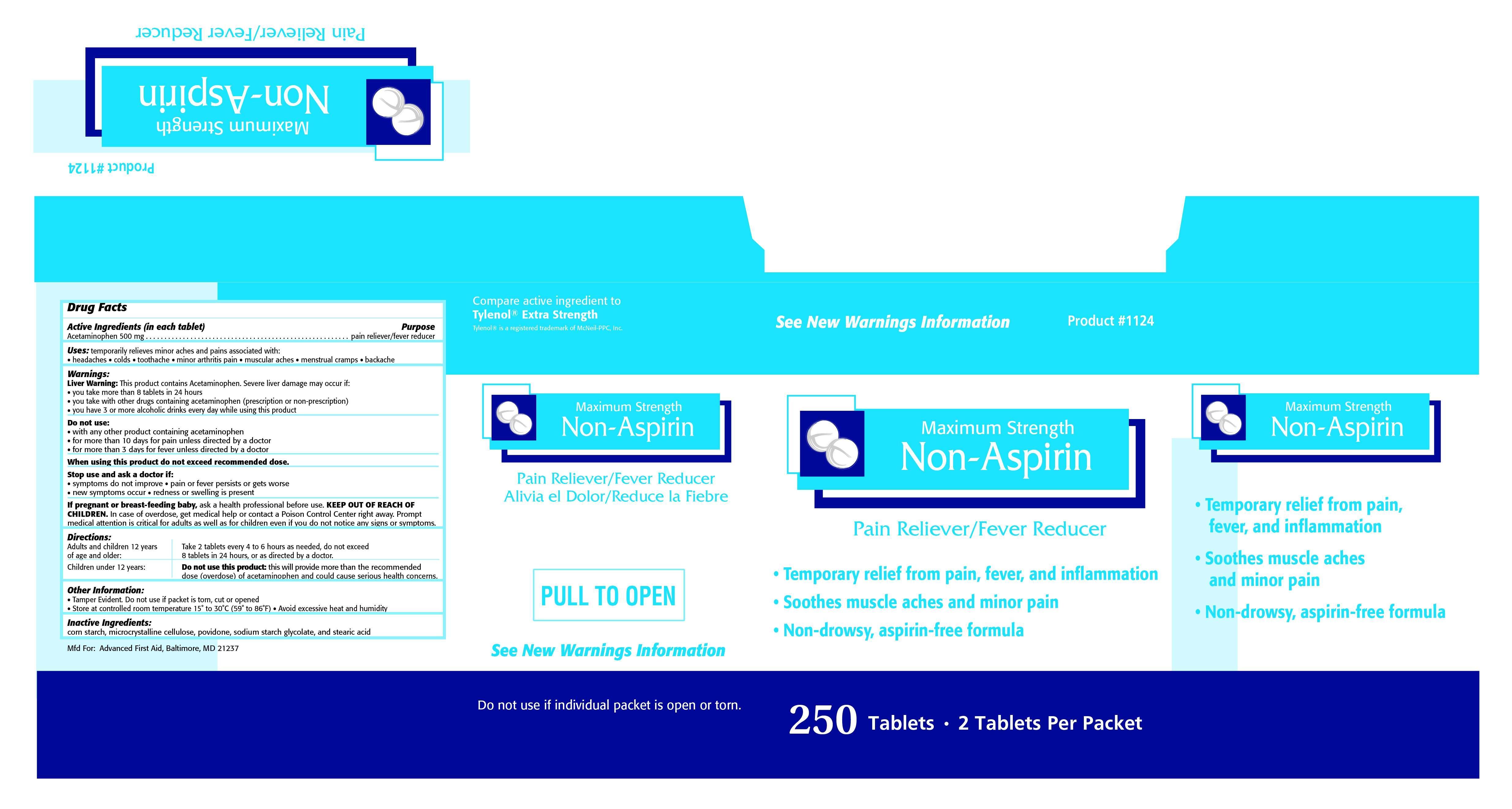 DRUG LABEL: NON-ASPIRIN
NDC: 67060-210 | Form: TABLET
Manufacturer: ADVANCED FIRST AID, INC.
Category: otc | Type: HUMAN OTC DRUG LABEL
Date: 20150410

ACTIVE INGREDIENTS: ACETAMINOPHEN 500 1/1 1
INACTIVE INGREDIENTS: STARCH, CORN; CELLULOSE, MICROCRYSTALLINE; POVIDONE; SODIUM STARCH GLYCOLATE TYPE A CORN; STEARIC ACID

ACTIVE INGREDIENT IN EACH TABLET-

Acetaminophen 500 mg

PURPOSE

pain reliever/fever reducer

INDICATIONS AND USAGE

Uses: temporarily relieves minor aches and pains associated with: • headaches • colds • toothache • minor arthritis pain • muscular aches • menstrual cramps • backache

Warnings:

Liver Warning: This product contains Acetaminophen. Severe liver damage may occur if: • you take more than 8 tablets in 24 hours • you take with other drugs containing acetaminophen (prescription or non-prescription) • you have 3 or more alcoholic drinks every day while using this product

Do not use: • with any other product containing acetaminophen • for more than 10 days for pain unless directed by a doctor • for more than 3 days for fever unless directed by a doctor

When using this product do not exceed recommended dose.

Stop use and ask a doctor if: • symptoms do not improve • pain or fever persists or gets worse • new symptoms occur • redness or swelling is present

PREGNANCY OR BREAST FEEDING

If pregnant or breast-feeding baby, ask a health professional before use.

KEEP OUT OF REACH OF CHILDREN. In case of overdose, get medical help or contact a Poison Control Center right away. Prompt medical attention is critical for adults as well as for children even if you do not notice any signs or symptoms.

Directions:

Adults and children 12 years of age and older: Take 2 tablets every 4 to 6 hours or as needed, do not exceed 8 tablets in 24 hours, or asdirected by a doctor.

Children under 12 years: Do not use this product: this will provide more than the recommended dose (overdose) of acetaminophen and could cause serious health concerns.

INACTIVE INGREDIENT

Inactive Ingredients: corn starch, microcrystalline cellulose, povidone, sodium starch glycolate, and stearic acid